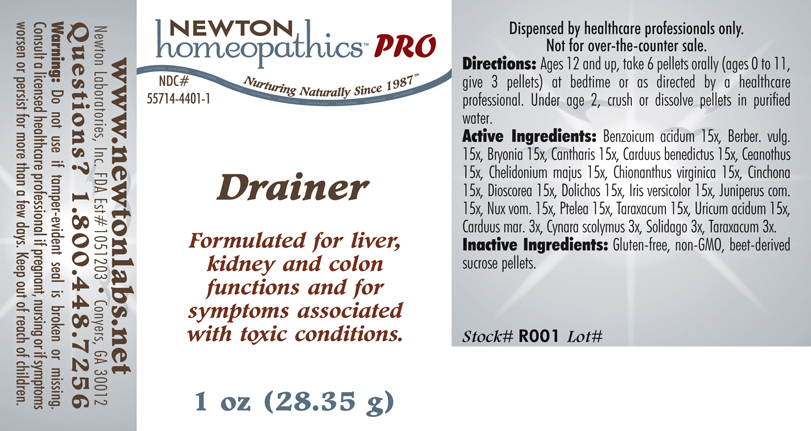 DRUG LABEL: Drainer 
NDC: 55714-4401 | Form: PELLET
Manufacturer: Newton Laboratories, Inc.
Category: homeopathic | Type: HUMAN PRESCRIPTION DRUG LABEL
Date: 20110601

ACTIVE INGREDIENTS: Benzoic Acid 15 [hp_X]/1 g; Berberis Vulgaris Root Bark 15 [hp_X]/1 g; Bryonia Alba Root 15 [hp_X]/1 g; Lytta Vesicatoria 15 [hp_X]/1 g; Centaurea Benedicta 15 [hp_X]/1 g; Ceanothus Americanus Leaf 15 [hp_X]/1 g; Chelidonium Majus 15 [hp_X]/1 g; Chionanthus Virginicus Bark 15 [hp_X]/1 g; Cinchona Officinalis Bark 15 [hp_X]/1 g; Dioscorea Villosa Tuber 15 [hp_X]/1 g; Mucuna Pruriens Fruit Trichome 15 [hp_X]/1 g; Iris Versicolor Root 15 [hp_X]/1 g; Juniper Berry 15 [hp_X]/1 g; Strychnos Nux-vomica Seed 15 [hp_X]/1 g; Ptelea Trifoliata Bark 15 [hp_X]/1 g; Taraxacum Officinale 15 [hp_X]/1 g; Uric Acid 15 [hp_X]/1 g; Silybum Marianum Seed 3 [hp_X]/1 g; Cynara Scolymus Leaf 3 [hp_X]/1 g; Solidago Virgaurea Flowering Top 3 [hp_X]/1 g
INACTIVE INGREDIENTS: Sucrose

Drainer

INDICATIONS & USAGE SECTION

Drainer: Formulated for liver, kidney and colon functions and for symptoms associated with toxic conditions.

DOSAGE & ADMINISTRATION SECTION

Directions: Ages 12 and up, take 6 pellets orally (ages 0 to 11, give 3 pellets) at bedtime or as directed by a healthcare professional. Under age 2, crush or dissolve pellets in purified water.

ACTIVE INGREDIENT SECTION

Benzoicum acidum 15x, Berber. vulg. 15x, Bryonia 15x, Cantharis 15x, Carduus benedictus 15x, Ceanothus 15x, Chelidonium majus 15x, Chionanthus virginica 15x, Cinchona 15x, Dioscorea 15x, Dolichos 15x, Iris versicolor 15x, Juniperus com.15x, Nux vom. 15x, Ptelea 15x, Taraxacum 15x, Uricum acidum 15x,Carduus mar. 3x, Cynara scolymus 3x, Solidago 3x, Taraxacum 3x.

INACTIVE INGREDIENT SECTION

Inactive Ingredients: Gluten-free, non-GMO, beet-derived sucrose pellets.

QUESTIONS? SECTION

www.newtonlabs.net Newton Laboratories, Inc. FDA Est # 1051203 - Conyers, GA 30012
Questions? 1.800.448.7256

WARNINGS SECTION

Warning: Do not use if tamper - evident seal is broken or missing. Consult a licensed healthcare professional if pregnant, nursing or if symptoms worsen or persist for more than a few days. Keep out of reach of children.

PREGNANCY OR BREAST FEEDING SECTION

Consult a licensed healthcare professional if pregnant or nursing or if symptoms worsen or persist for more than a few days.

KEEP OUT OF REACH OF CHILDREN SECTION

Keep out of reach of children.